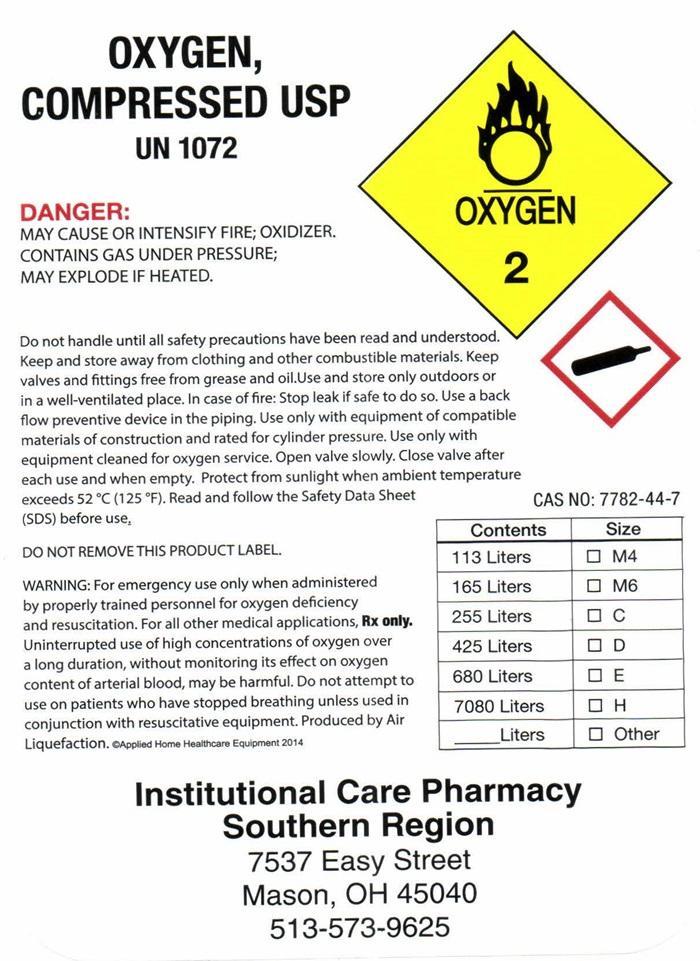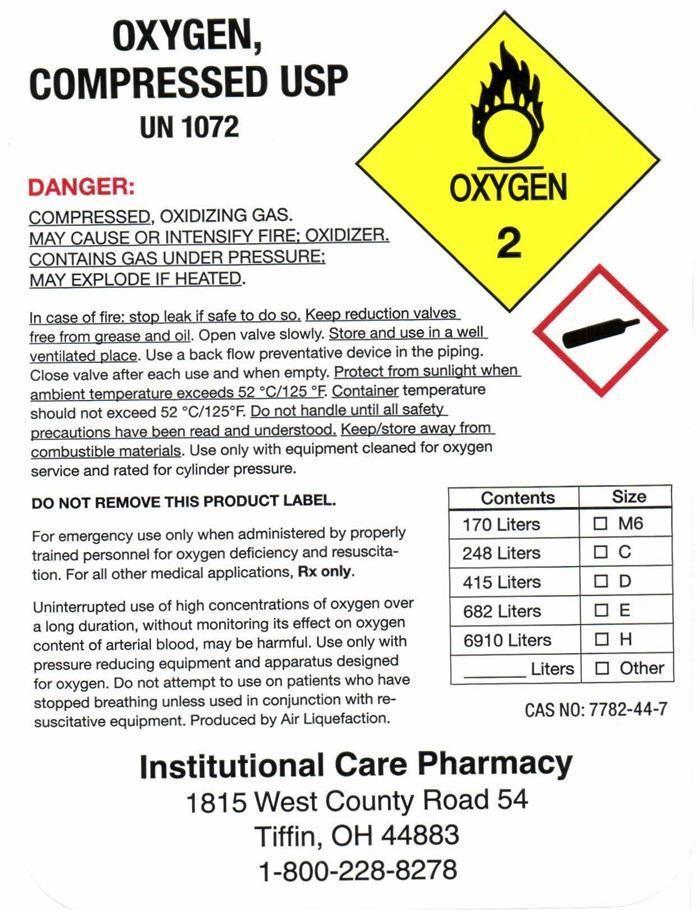 DRUG LABEL: OXYGEN
NDC: 44363-1815 | Form: GAS
Manufacturer: Institutional Care Pharmacy
Category: prescription | Type: HUMAN PRESCRIPTION DRUG LABEL
Date: 20251024

ACTIVE INGREDIENTS: OXYGEN 99 L/100 L

Oxygen

Oxygen Compressed USP Label

OXYGEN, COMPRESSED USP UN1072 OXYGEN 2

DANGER: COMPRESSED, OXIIZING GAS, MAY CAUSE OR INTENSIFY FIRE; OXIDIZER, CONTAINS GAS UNDER PRESSURE; MAY EXPLODE IF HEATED.

In case of fire: stop leak if safe to do so. Keep reduction valves free from grease and oil. Open valve slowly. Store and use in a well-ventilated place. Use a back-flow preventative device in the piping. Close valve after each use and when empty. Protect from sunlight when ambient temperature exceeds 52° C/125° F. Container temperature should not exceed 52° C/125° F. Do not handle until all safety precautions have been read and understood. Keep/store away from combustible materials. Use only with equipment cleaned for oxygen service and rated for cylinder pressure.

DO NOT REMOVE THIS PRODUCT LABEL.

For emergency use only when administered by properly trained personnel for oxygen deficiency and resuscitation. For all other medical applications. Rx only.

Uninterrupted use of high concentrations of oxygen over a long duration without monitoring its effect on oxygen content of arterial blood, may be harmful. Use only with pressure reducing equipment and apparatus designed for oxygen. Do not attempt to use on patients who have stopped breathing unless used in conjunction with resuscitative equipment. Produced by Air Liquefaction.

Contents Size

170 Liters __M6

248 Liters __ C

415 Liters __ D

682 Liters __ E

6910 Liters __ H

___ Liters __ Other

CAS 7782-44-7

Institutional Care Pharmacy

1815 West County Road 54

Tiffin, OH 44883

1-800-228-8278

res

Oxygen Label

OXYGEN, COMPRESSED USP UN1072 OXYGEN 2

DANGER: COMPRESSED, OXIIZING GAS, MAY CAUSE OR INTENSIFY FIRE; OXIDIZER, CONTAINS GAS UNDER PRESSURE; MAY EXPLODE IF HEATED.

In case of fire: stop leak if safe to do so. Keep reduction valves free from grease and oil. Open valve slowly. Store and use in a well-ventilated place. Use a back-flow preventative device in the piping. Close valve after each use and when empty. Protect from sunlight when ambient temperature exceeds 52° C/125° F. Container temperature should not exceed 52° C/125° F. Do not handle until all safety precautions have been read and understood. Keep/store away from combustible materials. Use only with equipment cleaned for oxygen service and rated for cylinder pressure.

DO NOT REMOVE THIS PRODUCT LABEL.

For emergency use only when administered by properly trained personnel for oxygen deficiency and resuscitation. For all other medical applications. Rx only.

Uninterrupted use of high concentrations of oxygen over a long duration without monitoring its effect on oxygen content of arterial blood, may be harmful. Use only with pressure reducing equipment and apparatus designed for oxygen. Do not attempt to use on patients who have stopped breathing unless used in conjunction with resuscitative equipment. Produced by Air Liquefaction.

Contents Size

170 Liters __M6

248 Liters __ C

415 Liters __ D

682 Liters __ E

6910 Liters __ H

___ Liters __ Other

CAS 7782-44-7

Institutional Care Pharmacy

Southern Region

7537 Easy Street

Mason, OH 45040

513-573-9625